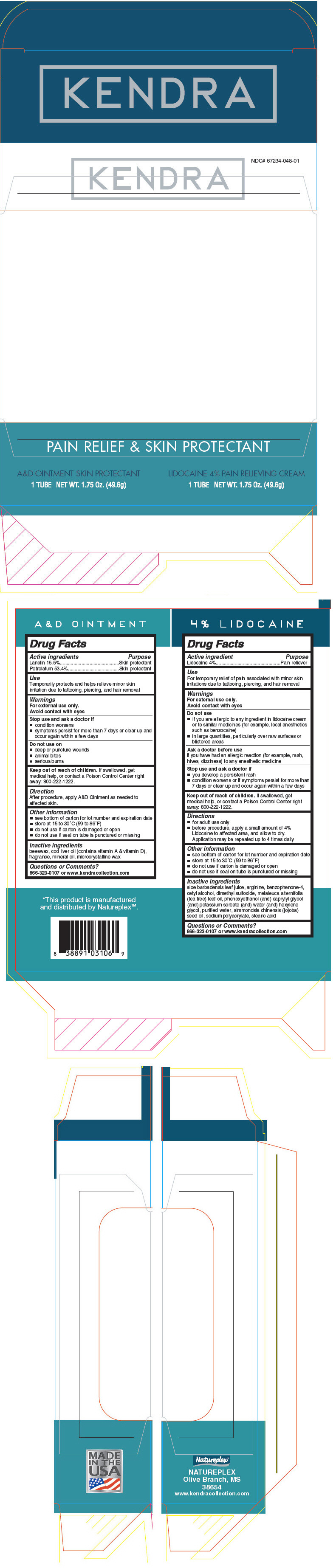 DRUG LABEL: Kendra SKIN PROTECTION and PAIN RELIEF FOR HAIR REMOVAL
NDC: 67234-048 | Form: KIT | Route: TOPICAL
Manufacturer: Natureplex, LLC
Category: otc | Type: HUMAN OTC DRUG LABEL
Date: 20171020

ACTIVE INGREDIENTS: Lanolin 155 mg/1 g; Petrolatum 534 mg/1 g; Lidocaine 40 mg/1 g
INACTIVE INGREDIENTS: YELLOW WAX; COD LIVER OIL; LIGHT MINERAL OIL; MICROCRYSTALLINE WAX; ALOE VERA LEAF; SULISOBENZONE; CETYL ALCOHOL; DIMETHYL SULFOXIDE; CAPRYLYL GLYCOL; ARGININE; WATER; JOJOBA OIL; SODIUM POLYACRYLATE (2500000 MW); STEARIC ACID; TEA TREE OIL

Kendra SKIN PROTECTION & PAIN RELIEF FOR HAIR REMOVAL

A&D OINTMENT

Drug Facts

ACTIVE INGREDIENT

Active ingredients | Purpose
Lanolin 15.5% | Skin Protectant
Petrolatum 53.4% | Skin protectant

Use

- temporarily protects and helps relieve minor skin irritation due to tattooing, piercing, and hair removal

Warnings

For external use only

When using this product

- do not get into eyes

Stop use and ask a doctor if

- condition worsens
- symptoms persist for more than 7 days or clear up and occur again within a few days

Do not use on

- deep or puncture wounds
- animal bites
- serious burns

Keep out of reach of children. If swallowed, get medical help, or contact a Poison Control Center immediately: 1-800-222-1222.

Directions

- After procedure, apply A&D Skin Protectant as needed to affected skin.

Other information

- see bottom of carton for lot number and expiration date
- store at 15 to 30°C (59 to 86°F)
- do not use if carton is damaged or open
- do not use if seal on tube is punctured or missing

Inactive ingredients

beeswax, cod liver oil (contains vitamin A & vitamin D), fragrance, light mineral oil, microcrystalline wax

Questions or Comments?

1-866-323-0107 or www.kendracollection.com

4% LIDOCAINE

Drug Facts

Active ingredient

Lidocaine 4%

Purpose

Pain Relieving Cream

Use

- for temporary relief of pain associated with minor skin irritations due to tattooing, piercing, and hair removal

Warnings

For external use only

Avoid contact with the eyes

Do Not Use

- if you are allergic to any ingredient in lidocaine cream or to similar medicines (e.g., local anesthetics such as benzocaine)
- in large quantities, particularly over raw surfaces or blistered areas

Ask a doctor before use

- if you have had an allergic reaction (e.g., rash, hives, dizziness) to any anesthetic medicine

Stop use and ask a doctor if

- you develop a persistent rash
- conditions worsens or if symptoms persist for more than 7 days or clear up and occur again within a few days

Keep out of reach of children. If swallowed, get medical help, or contact a Poison Control Center immediately: 1-800-222-1222.

Directions

- For adult use only.
- Before procedure, apply a small amount of pain relieving cream to affected area, and allow to dry. Application may be repeated up to 4 times daily.

Other information

- see bottom of carton for lot number and expiration date
- store at 15 to 30°C (59 to 86°F)
- do not use if carton is damaged or open
- do not use if seal on tube is punctured or missing

Inactive ingredients

aloe barbadensis leaf juice, benzophenone-4, cetyl alcohol, dimethyl sulfoxide, jeecide cap-5, L-arginine, purified water, simmondsia chinesis (jojoba) seed oil, sodium polyacrylate, stearic acid, tea tree oil

Questions or Comments?

1-866-323-0107 or www.kendracollection.com

This product
is manufactured
and distributed
by Natureplex™.

PRINCIPAL DISPLAY PANEL - Kit Carton

NDC# 67234-048-01

KENDRA

PAIN RELIEF & SKIN PROTECTANT

A&D OINTMENT SKIN PROTECTANT
1 TUBE NET WT. 1.75 Oz. (49.6g)

LIDOCAINE 4% PAIN RELIEVING CREAM
1 TUBE NET WT. 1.75 Oz. (49.6g)